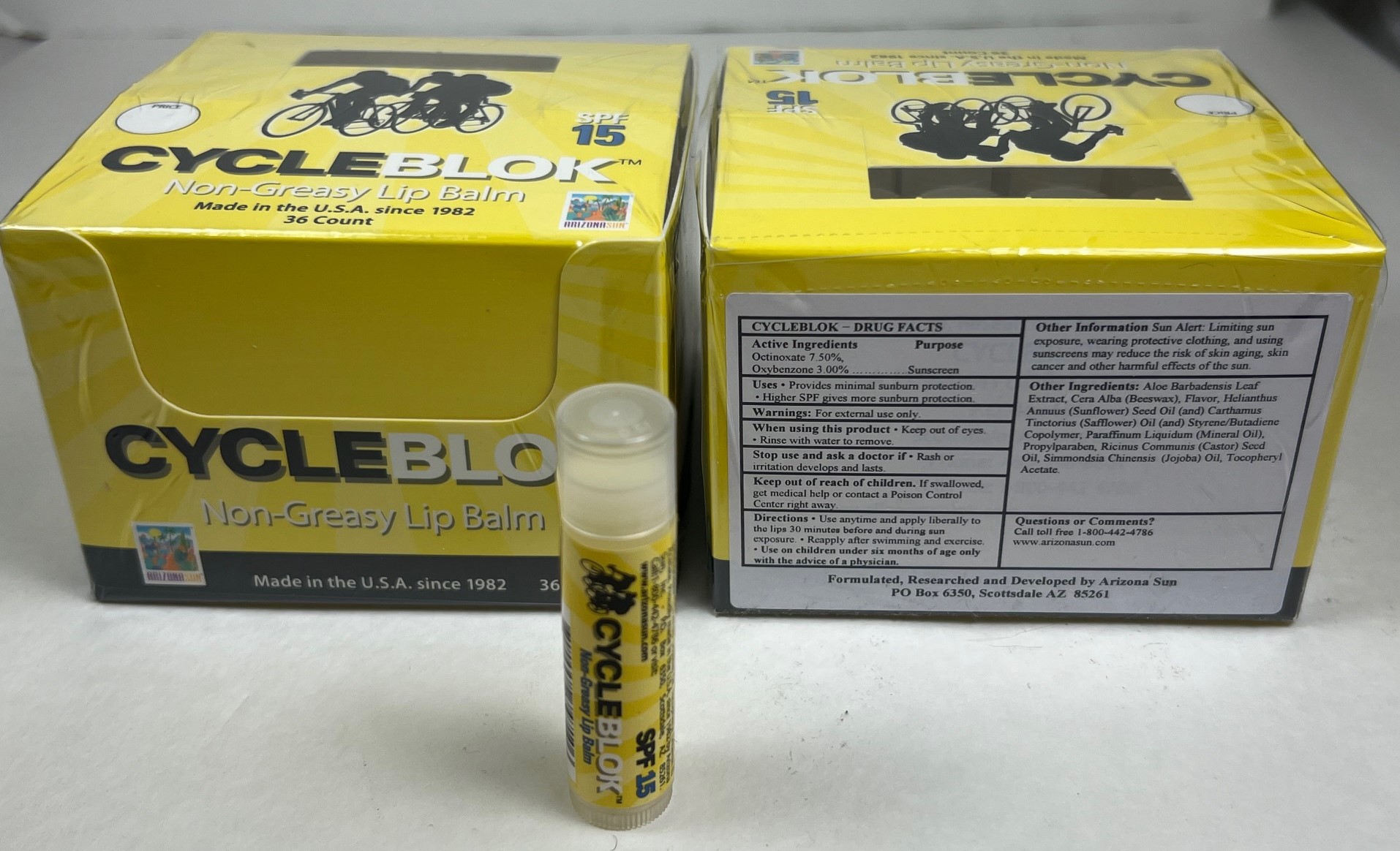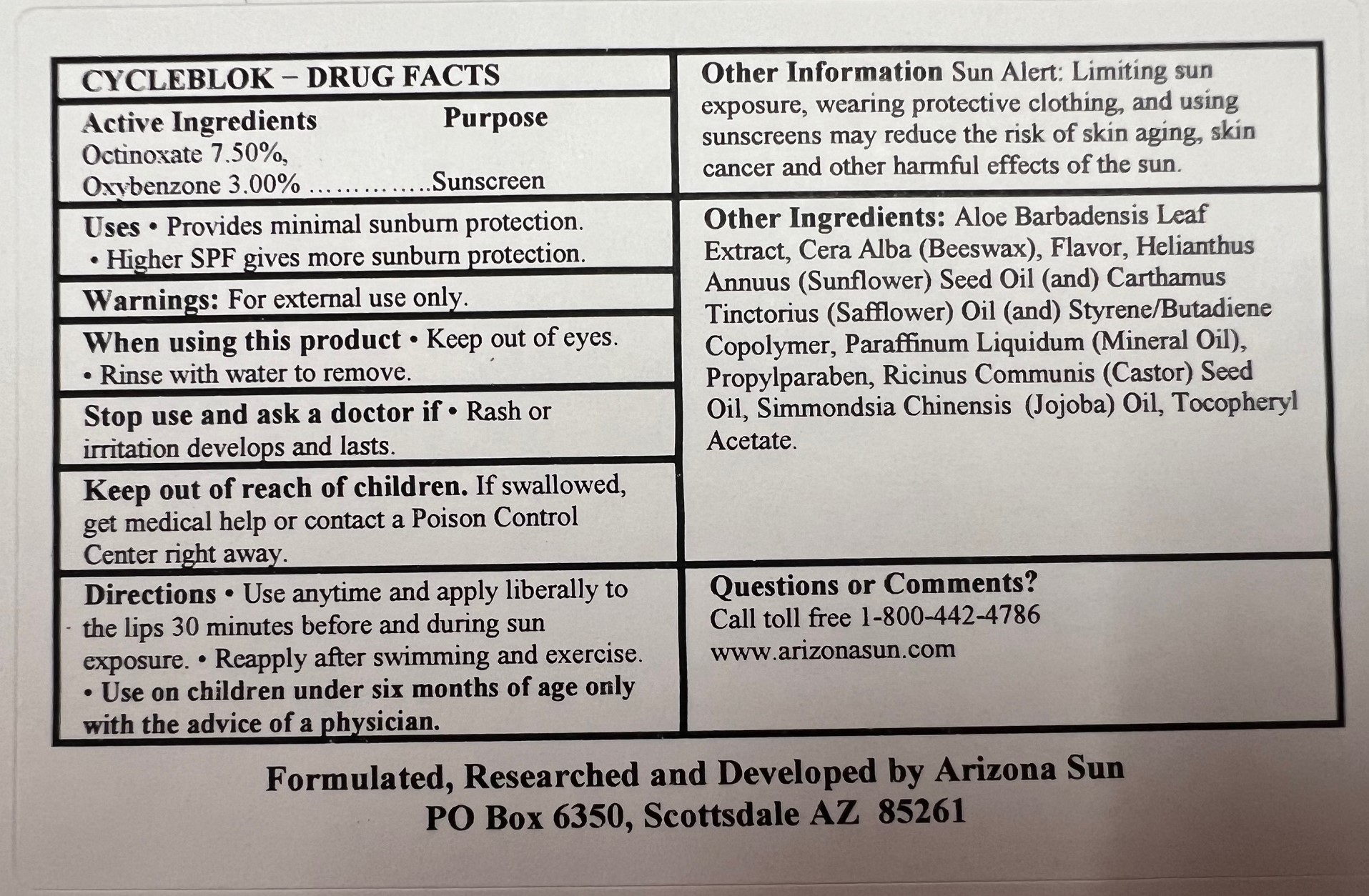 DRUG LABEL: Arizona Sun Products Cycleblok Lip Balm SPF 15
NDC: 61973-404 | Form: LIPSTICK
Manufacturer: Arizona Sun Products
Category: otc | Type: HUMAN OTC DRUG LABEL
Date: 20240222

ACTIVE INGREDIENTS: OXYBENZONE 30 mg/1 g; OCTINOXATE 75 mg/1 g
INACTIVE INGREDIENTS: SAFFLOWER OIL; SUNFLOWER SEED; MINERAL OIL; SIMMONDSIA CHINENSIS SEED; WHITE WAX; CASTOR OIL; .ALPHA.-TOCOPHEROL ACETATE; ALOE VERA LEAF; PROPYLPARABEN

Cycleblok Lipbalm Box

Active Ingredients

Octinoxate 7.50%, Oxybenzone 3.00%

Purpose

Sunscreen

Uses

Provides minimal sunburn protection. Higher SPF gives more sunburn protection

Warnings

For external use only.

When using this product

keep out of eyes. Rinse with water to remove.

Stop use and ask a doctor

if rash or irritation develops and lasts.

Keep out of the reach of children.

If swallowed get medical help or contact a poison control center right away.

Directions

Use anytime and apply liberally to the lips 30 minutes before and during sun exposure. Reapply after swimming and exercise. Use on children under the age of six months only wih the advise of a physician.

Other Information

Sun Alert: Limiting sun exposure, wearing protective clothing, and using suscreen may reduce the risk of skin aging, skin cancer and other harmful effects of the sun.

Inactive Ingredients

Aloe Barbadensis Leaf Extract, Cera Alba (Beeswax), Flavor, Helianthus Annuus (Sunflower) Seed Oil (and) Carthamus Tinctorius (Safflower) Oil (and) Styrene/Butadiene Copolymer, Paraffinum Liquidum (Mineral Oil), Propylparaben, Ricinus Communis (Castor) Seed Oil, Simmondsia Chinensis (Jojoba) Oil, Tocopheryl Acetate (Vitamin E).

Questions or Comments?

Call toll free 1-800-442-4786